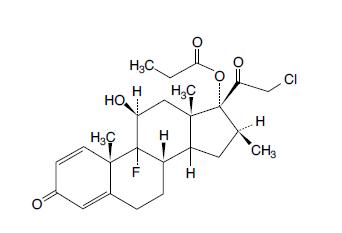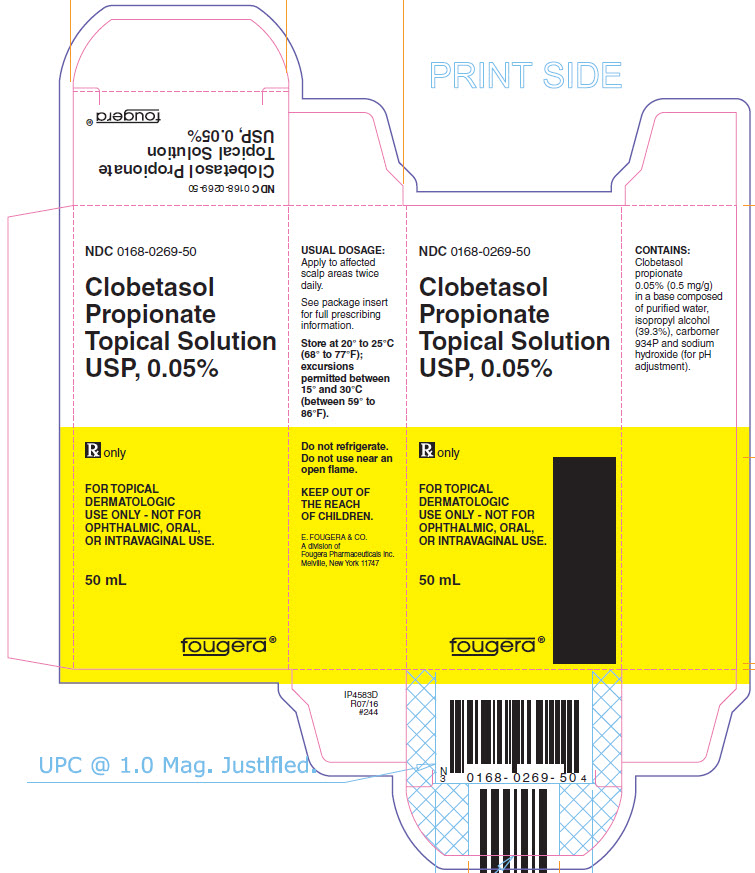 DRUG LABEL: Clobetasol Propionate
NDC: 0168-0269 | Form: SOLUTION
Manufacturer: E. Fougera & Co. a division of Fougera Pharmaceuticals, LLC
Category: prescription | Type: HUMAN PRESCRIPTION DRUG LABEL
Date: 20260128

ACTIVE INGREDIENTS: clobetasol propionate 0.5 mg/1 mL
INACTIVE INGREDIENTS: isopropyl alcohol; sodium hydroxide; water; CARBOMER HOMOPOLYMER TYPE B (ALLYL SUCROSE CROSSLINKED)

Clobetasol Propionate
Topical Solution USP, 0.05%

Rx only

FOR TOPICAL DERMATOLOGIC USE ONLY - NOT FOR OPHTHALMIC, ORAL, OR INTRAVAGINAL USE.

DESCRIPTION:

Clobetasol propionate topical solution USP, 0.05% contains the active compound clobetasol propionate, a synthetic corticosteroid for topical dermatologic use. Clobetasol, an analog of prednisolone, has a high degree of glucocorticoid activity and a slight degree of mineralocorticoid activity.

Chemically, clobetasol propionate is 21-chloro-9-fluoro-11β,17-dihydroxy-16β-methylpregna-1,4-diene-3,20-dione 17-propionate, and it has the following structural formula:

Clobetasol propionate has the molecular formula C25H32ClFO5 and a molecular weight of 466.98. It is a white to cream-colored crystalline powder insoluble in water.

Clobetasol propionate topical solution USP, 0.05% contains: 0.5 mg/g clobetasol propionate in a base composed of purified water, isopropyl alcohol (39.3%), carbomer 934P and sodium hydroxide (for pH adjustment).

CLINICAL PHARMACOLOGY:

The corticosteroids are a class of compounds comprising steroid hormones secreted by the adrenal cortex and their synthetic analogs. In pharmacologic doses, corticosteroids are used primarily for their anti-inflammatory and/or immunosuppressive effects. Topical corticosteroids such as clobetasol propionate are effective in the treatment of corticosteroid-responsive dermatoses primarily because of their anti-inflammatory, antipruritic, and vasoconstrictive actions. However, while the physiologic, pharmacologic, and clinical effects of the corticosteroids are well known, the exact mechanisms of their actions in each disease are uncertain.

Clobetasol propionate, a corticosteroid, has been shown to have topical (dermatologic) and systemic pharmacologic and metabolic effects characteristic of this class of drugs.

Pharmacokinetics: The extent of percutaneous absorption of topical corticosteroids, including clobetasol propionate, is determined by many factors, including the vehicle, the integrity of the epidermal barrier, and the use of occlusive dressings (see DOSAGE AND ADMINISTRATION).

As with all topical corticosteroids, clobetasol propionate can be absorbed from normal intact skin. Inflammation and/or other disease processes in the skin may increase percutaneous absorption. Occlusive dressings substantially increase the percutaneous absorption of topical corticosteroids (see DOSAGE AND ADMINISTRATION).

Once absorbed through the skin, topical corticosteroids enter pharmacokinetic pathways similarly to systemically administered corticosteroids. Corticosteroids are bound to plasma proteins in varying degrees. Corticosteroids are metabolized primarily in the liver and are then excreted by the kidneys. Some of the topical corticosteroids, including clobetasol propionate and its metabolites, are also excreted into the bile.

Following repeated nonocclusive application in the treatment of scalp psoriasis, there is some evidence that clobetasol propionate topical solution, 0.05% has the potential to depress plasma cortisol levels in some patients. However, hypothalamic-pituitary-adrenal (HPA) axis effects produced by systemically absorbed clobetasol propionate have been shown to be transient and reversible upon completion of a 2-week course of treatment.

INDICATIONS AND USAGE:

Clobetasol propionate topical solution USP, 0.05% is indicated for short-term topical treatment of inflammatory and pruritic manifestations of moderate to severe corticosteroid-responsive dermatoses of the scalp. Treatment beyond 2 consecutive weeks is not recommended, and the total dosage should not exceed 50 mL/week because of the potential for the drug to suppress the HPA axis.

This product is not recommended for use in pediatric patients under 12 years of age.

CONTRAINDICATIONS:

Clobetasol propionate topical solution is contraindicated in patients with primary infections of the scalp, or in patients who are hypersensitive to clobetasol propionate, other corticosteroids, or any ingredient in this preparation.

PRECAUTIONS:

GENERAL PRECAUTIONS

General: Clobetasol propionate is a highly potent topical corticosteroid that has been shown to suppress the HPA axis at doses as low as 2 g (of ointment) per day.

Systemic absorption of topical corticosteroids has resulted in reversible HPA axis suppression, manifestations of Cushing's syndrome, hyperglycemia, and glucosuria in some patients.

Conditions that augment systemic absorption include the application of the more potent corticosteroids, use over large surface areas, prolonged use, and the addition of occlusive dressings. Therefore, patients receiving a large dose of a potent topical steroid applied to a large surface area should be evaluated periodically for evidence of HPA axis suppression by using the urinary free cortisol and ACTH-stimulation tests. If HPA axis suppression is noted, an attempt should be made to withdraw the drug, to reduce the frequency of application, or to substitute a less potent steroid.

Recovery of HPA axis function is generally prompt and complete upon discontinuation of the drug. Infrequently, signs and symptoms of steroid withdrawal may occur, requiring supplemental systemic corticosteroids.

Pediatric patients may absorb proportionally larger amounts of topical corticosteroids and thus be more susceptible to systemic toxicity (see PRECAUTIONS: Pediatric Use).

If irritation develops, topical corticosteroids should be discontinued and appropriate therapy instituted. Irritation is possible if clobetasol propionate topical solution contacts the eye. If that should occur, immediate flushing of the eye with a large volume of water is recommended.

If the inflammatory lesion becomes infected, the use of an appropriate antifungal or antibacterial agent should be instituted. If a favorable response does not occur promptly, the corticosteroid should be discontinued until the infection has been adequately controlled.

Although clobetasol propionate topical solution is intended for the treatment of inflammatory conditions of the scalp, it should be noted that certain areas of the body, such as the face, groin, and axillae, are more prone to atrophic changes than other areas of the body following treatment with corticosteroids. Frequent observation of the patient is important if these areas are to be treated.

As with other potent topical corticosteroids, clobetasol propionate topical solution should not be used in the treatment of rosacea and perioral dermatitis. Topical corticosteroids in general should not be used in the treatment of acne or as sole therapy in widespread plaque psoriasis.

PATIENT COUNSELING INFORMATION

Information for Patients: Patients using clobetasol propionate topical solution should receive the following information and instructions:

1. This medication is to be used as directed by the physician and should not be used longer than the prescribed time period. It is for external use only. Avoid contact with the eyes.
2. This medication should not be used for any disorder other than that for which it was prescribed.
3. The treated skin area should not be bandaged or otherwise covered or wrapped so as to be occlusive.
4. Patients should report any signs of local adverse reactions to the physician.

LABORATORY TESTS

Laboratory Tests: The following tests may be helpful in evaluating patients for HPA axis suppression:

Urinary free cortisol test

ACTH stimulation test

CARCINOGENESIS AND MUTAGENESIS AND IMPAIRMENT OF FERTILITY

Carcinogenesis, Mutagenesis, Impairment of Fertility: Long-term animal studies have not been performed to evaluate the carcinogenic potential of clobetasol propionate.

Studies in the rat following subcutaneous administration at dosage levels up to 50 mcg/kg/day revealed that the females exhibited an increase in the number of resorbed embryos and a decrease in the number of living fetuses at the highest dose.

Clobetasol propionate was nonmutagenic in 3 different test systems: the Ames test, the Saccharomyces cerevisiae gene conversion assay and the E. coli B WP2 fluctuation test.

PREGNANCY

Pregnancy: Teratogenic effects - Corticosteroids have been shown to be teratogenic in laboratory animals when administered systemically at relatively low dosage levels. Some corticosteroids have been shown to be teratogenic after dermal application to laboratory animals.

Clobetasol propionate has not been tested for teratogenicity when applied topically; however, it is absorbed percutaneously, and when administered subcutaneously it was a significant teratogen in both the rabbit and the mouse. Clobetasol propionate has greater teratogenic potential than steroids that are less potent.

Teratogenicity studies in mice using the subcutaneous route resulted in fetotoxicity at the highest dose tested (1 mg/kg) and teratogenicity at all dose levels tested down to 0.03 mg/kg. These doses are approximately 1.4 and 0.04 times, respectively, the human topical dose of clobetasol propionate topical solution. Abnormalities seen included cleft palate and skeletal abnormalities.

In rabbits, clobetasol propionate was teratogenic at doses of 3 and 10 mcg/kg. These doses are approximately 0.02 and 0.05 times, respectively, the human topical dose of clobetasol propionate topical solution. Abnormalities seen included cleft palate, cranioschisis, and other skeletal abnormalities.

There are no adequate and well-controlled studies of the teratogenic potential of clobetasol propionate in pregnant women. Clobetasol propionate topical solution should be used during pregnancy only if the potential benefit justifies the potential risk to the fetus.

NURSING MOTHERS

Nursing Mothers: Systemically administered corticosteroids appear in human milk and could suppress growth, interfere with endogenous corticosteroid production, or cause other untoward effects. It is not known whether topical administration of corticosteroids could result in sufficient systemic absorption to produce detectable quantities in human milk. Because many drugs are excreted in human milk, caution should be exercised when clobetasol propionate topical solution is administered to a nursing woman.

PEDIATRIC USE

Pediatric Use: Use of clobetasol propionate topical solution in pediatric patients under 12 years of age is not recommended.

Pediatric patients may demonstrate greater susceptibility to topical corticosteroid-induced HPA axis suppression and Cushing’s syndrome than mature patients because of a larger skin surface area to body weight ratio.

HPA axis suppression, Cushing’s syndrome, linear growth retardation, delayed weight gain, and intracranial hypertension have been reported in children receiving topical corticosteroids. Manifestations of adrenal suppression in children include low plasma cortisol levels, and an absence of response to ACTH stimulation. Manifestations of intracranial hypertension include bulging fontanelles, headaches, and bilateral papilledema.

GERIATRIC USE

Geriatric Use: A limited number of patients at or above 65 years of age (n = 65) have been treated with clobetasol propionate topical solution in US and non-US clinical trials. While the number of patients is too small to permit separate analysis of efficacy and safety, the adverse reactions reported in this population were similar to those reported by younger patients. Based on available data, no adjustment of dosage of clobetasol propionate topical solution in geriatric patients is warranted.

ADVERSE REACTIONS:

Clobetasol propionate topical solution is generally well tolerated when used for 2-week treatment periods.

The most frequent adverse events reported for clobetasol propionate topical solution have been local and have included burning and/or stinging sensation, which occurred in 29 of 294 patients; scalp pustules, which occurred in 3 of 294 patients; and tingling and folliculitis, each of which occurred in 2 of 294 patients. Less frequent adverse events were itching and tightness of the scalp, dermatitis, tenderness, headache, hair loss, and eye irritation, each of which occurred in 1 of 294 patients.

The following local adverse reactions are reported infrequently when topical corticosteroids are used as recommended. These reactions are listed in an approximately decreasing order of occurrence: burning, itching, irritation, dryness, folliculitis, hypertrichosis, acneiform eruptions, hypopigmentation, perioral dermatitis, allergic contact dermatitis, maceration of the skin, secondary infection, skin atrophy, striae, and miliaria. Systemic absorption of topical corticosteroids has produced reversible HPA axis suppression, manifestations of Cushing's syndrome, hyperglycemia, and glucosuria in some patients. In rare instances, treatment (or withdrawal of treatment) of psoriasis with corticosteroids is thought to have exacerbated the disease or provoked the pustular form of the disease, so careful patient supervision is recommended.

To report SUSPECTED ADVERSE REACTIONS, contact Fougera Pharmaceuticals Inc., at 1-800-645-9833 or FDA at 1-800-FDA-1088 or www.fda.gov/medwatch.

OVERDOSAGE:

Topically applied clobetasol propionate topical solution can be absorbed in sufficient amounts to produce systemic effects (see PRECAUTIONS).

DOSAGE AND ADMINISTRATION:

Clobetasol propionate topical solution USP, 0.05% should be applied to the affected scalp areas twice daily, once in the morning and once at night.

Clobetasol propionate topical solution USP, 0.05% is potent; therefore, treatment should be limited to 2 consecutive weeks, and amounts greater than 50 mL/week should not be used.

Clobetasol propionate topical solution USP, 0.05% is not to be used with occlusive dressings.

Geriatric Use: In studies where geriatric patients (65 years of age or older, see PRECAUTIONS) have been treated with clobetasol propionate topical solution, safety did not differ from that in younger patients; therefore, no dosage adjustment is recommended.

HOW SUPPLIED:

Clobetasol Propionate Topical Solution USP, 0.05% is supplied in plastic squeeze bottle as follows:

NDC 0168-0269-50 50 mL plastic bottle

Store at 20°C to 25°C (68°F to 77°F), excursions permitted between 15°C and 30°C (59°F to 86°F). [See USP Controlled Room Temperature].

Do not refrigerate. Do not use near an open flame.

KEEP OUT OF THE REACH OF CHILDREN.

E. FOUGERA & CO.
A division of
FOUGERA
PHARMACEUTICALS INC.
Melville, New York 11747

46258829A
R10/2019
#244

PACKAGE LABEL – PRINCIPAL DISPLAY PANEL – 50 mL CARTON

NDC 0168-0269-50

Fougera®

CLOBETASOL
PROPIONATE
TOPICAL
SOLUTION
USP, 0.05%

50 mL

FOR TOPICAL
DERMATOLOGIC
USE ONLY NOT FOR
OPHTHALMIC, ORAL,
OR INTRAVAGINAL USE.

Rx only

E. FOUGERA & CO.
A division of
Fougera Pharmaceuticals Inc.
Melville, New York 11747